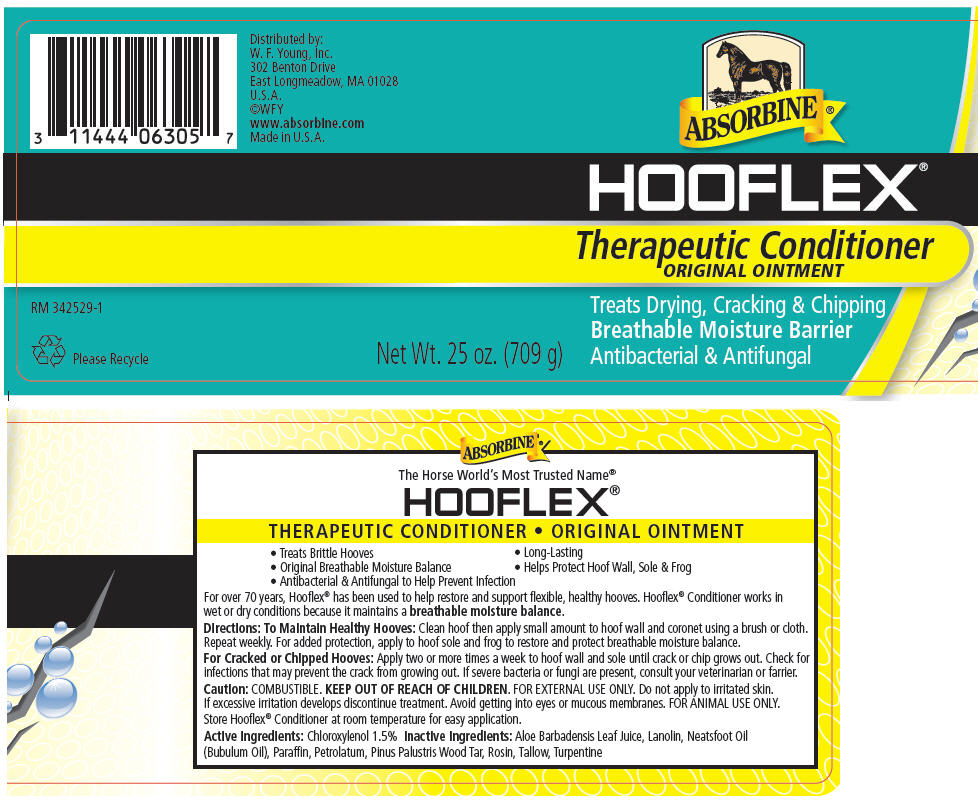 DRUG LABEL: Absorbine Hooflex 
NDC: 11444-063 | Form: OINTMENT
Manufacturer: W. F. Young, Inc.
Category: animal | Type: OTC ANIMAL DRUG LABEL
Date: 20160623

ACTIVE INGREDIENTS: CHLOROXYLENOL 1.5 g/100 g

ABSORBINE® HOOFLEX® Therapeutic Conditioner ORIGINAL OINTMENT

VETERINARY INDICATIONS

- Treats Brittle Hooves
- Original Breathable Moisture Balance
- Antibacterial & Antifungal to Help Prevent Infection
- Long-Lasting
- Helps Protect Hoof Wall, Sole & Frog

DESCRIPTION

For over 70 years, Hooflex® has been used to help restore and support flexible, healthy hooves. Hooflex® Conditioner works in wet or dry conditions because it maintains a breathable moisture balance.

Directions

To Maintain Healthy Hooves

Clean hoof then apply small amount to hoof wall and coronet using a brush or cloth. Repeat weekly. For added protection, apply to hoof sole and frog to restore and protect breathable moisture balance.

For Cracked or Chipped Hooves

Apply two or more times a week to hoof wall and sole until crack or chip grows out. Check for infections that may prevent the crack from growing out. If severe bacteria or fungi are present, consult your veterinarian or farrier.

Caution

COMBUSTIBLE. KEEP OUT OF REACH OF CHILDREN. FOR EXTERNAL USE ONLY. Do not apply to irritated skin. If excessive irritation develops discontinue treatment. Avoid getting into eyes or mucous membranes. FOR ANIMAL USE ONLY.

STORAGE AND HANDLING

Store Hooflex® Conditioner at room temperature for easy application.

Active Ingredients

Chloroxylenol 1.5%

Inactive Ingredients

Aloe Barbadensis Leaf Juice, Lanolin, Neatsfoot Oil (Bubulum Oil), Paraffin, Petrolatum, Pinus Palustris Wood Tar, Rosin, Tallow, Turpentine

Distributed by:
W. F. Young, Inc.
302 Benton Drive
East Longmeadow, MA 01028

PRINCIPAL DISPLAY PANEL - 709 g Jar Label

ABSORBINE®

HOOFLEX®

Therapeutic Conditioner
ORIGINAL OINTMENT

Treats Drying, Cracking & Chipping
Breathable Moisture Barrier
Antibacterial & Antifungal

Net Wt. 25 oz. (709 g)